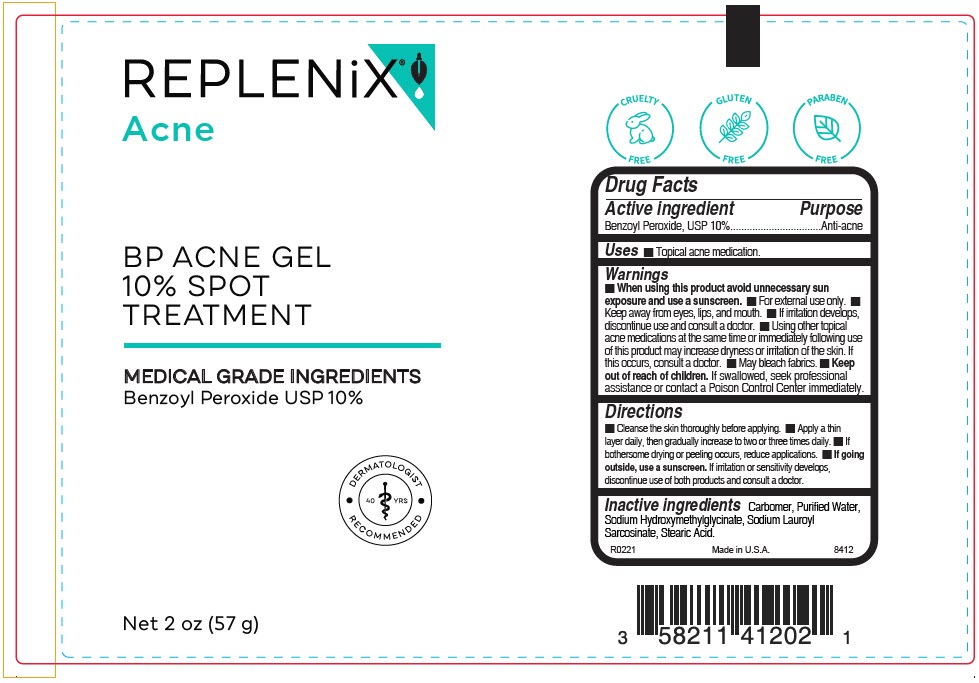 DRUG LABEL: Replenix BP Acne
NDC: 51326-841 | Form: GEL
Manufacturer: Topiderm, Inc.
Category: otc | Type: HUMAN OTC DRUG LABEL
Date: 20240618

ACTIVE INGREDIENTS: BENZOYL PEROXIDE 100 mg/1 g
INACTIVE INGREDIENTS: WATER; CARBOMER COPOLYMER TYPE A (ALLYL PENTAERYTHRITOL CROSSLINKED); SODIUM LAUROYL SARCOSINATE; SODIUM HYDROXYMETHYLGLYCINATE; STEARIC ACID

Replenix® BP Acne

Drug Facts

Active ingredient

Benzoyl Peroxide, USP 10%

Purpose

Anti-acne

Uses

- Topical acne medication.

Warnings

- When using this product avoid unnecessary sun exposure and use a sunscreen.

- For external use only.
- Keep away from eyes, lips, and mouth.
- If irritation develops, discontinue use and consult a doctor.
- Using other topical acne medications at the same time or immediately following use of this product may increase dryness or irritation of the skin. If this occurs, consult a doctor.
- May bleach fabrics.

- Keep out of reach of children. If swallowed, seek professional assistance or contact a Poison Control Center immediately.

Directions

- Cleanse the skin thoroughly before applying.
- Apply a thin layer daily, then gradually increase to two or three times daily.
- If bothersome drying or peeling occurs, reduce applications.
- If going outside, use a sunscreen. If irritation or sensitivity develops, discontinue use of both products and consult a doctor.

Inactive ingredients

Carbomer, Purified Water, Sodium Hydroxymethylglycinate, Sodium Lauroyl Sarcosinate, Stearic Acid.

PRINCIPAL DISPLAY PANEL - 57 g Bottle Label

REPLENiX®
Acne

BP ACNE GEL
10% SPOT
TREATMENT

MEDICAL GRADE INGREDIENTS
Benzoyl Peroxide USP 10%

DERMATOLOGIST
• RECOMMENDED •

40 YRS

Net 2 oz (57 g)